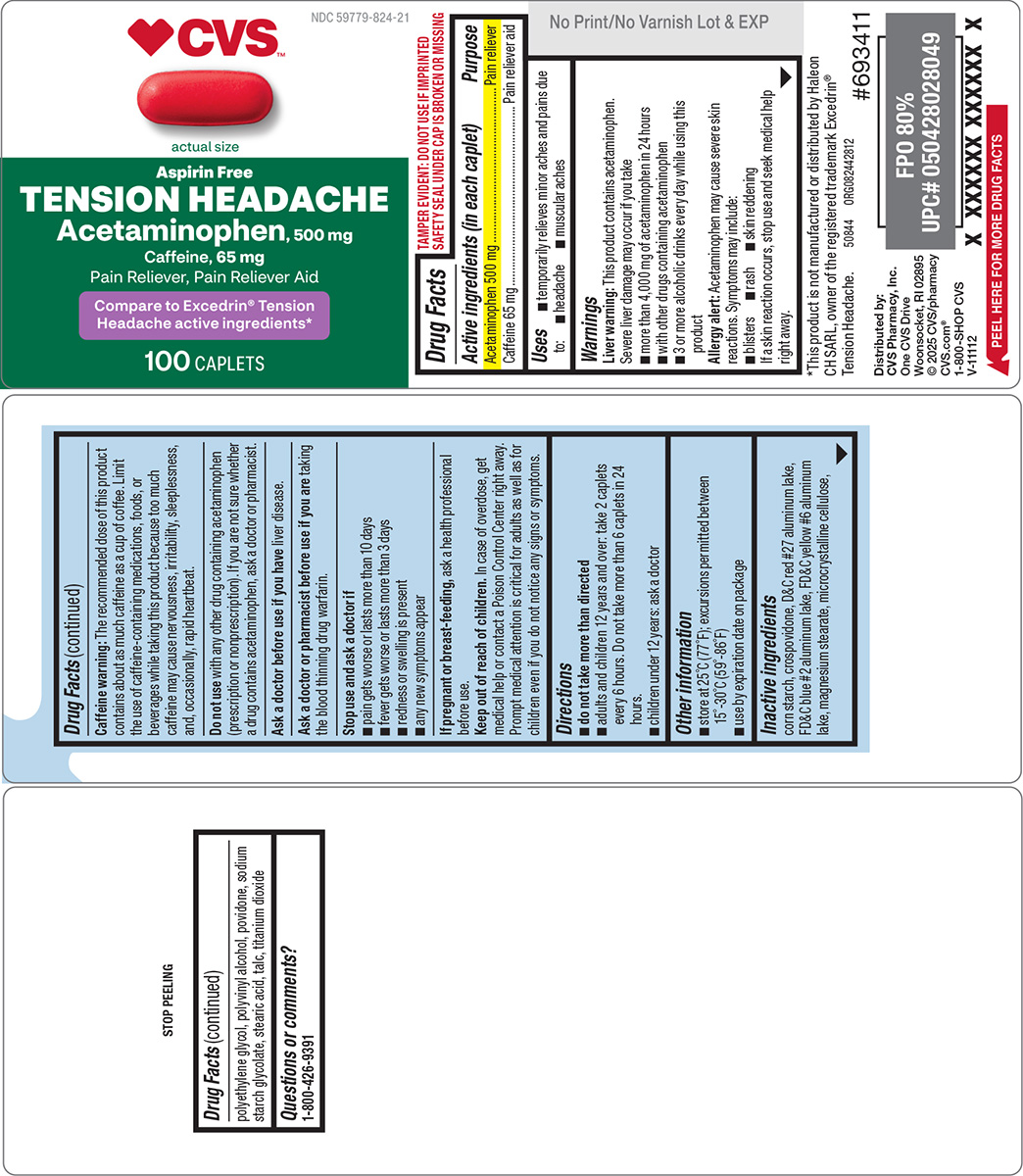 DRUG LABEL: Tension Headache
NDC: 59779-824 | Form: TABLET, FILM COATED
Manufacturer: CVS Pharmacy
Category: otc | Type: HUMAN OTC DRUG LABEL
Date: 20250925

ACTIVE INGREDIENTS: ACETAMINOPHEN 500 mg/1 1; CAFFEINE 65 mg/1 1
INACTIVE INGREDIENTS: STARCH, CORN; CROSPOVIDONE; D&C RED NO. 27 ALUMINUM LAKE; FD&C BLUE NO. 2 ALUMINUM LAKE; FD&C YELLOW NO. 6 ALUMINUM LAKE; MAGNESIUM STEARATE; MICROCRYSTALLINE CELLULOSE; POLYETHYLENE GLYCOL, UNSPECIFIED; POLYVINYL ALCOHOL, UNSPECIFIED; POVIDONE, UNSPECIFIED; SODIUM STARCH GLYCOLATE TYPE A POTATO; STEARIC ACID; TALC; TITANIUM DIOXIDE

CVS 44-428

Active ingredients (in each caplet)

Acetaminophen 500 mg
Caffeine 65 mg

Purpose

Pain reliever
Pain reliever aid

Uses

- temporarily relieves minor aches and pains due to:
  - headache
  - muscular aches

Warnings

Liver warning: This product contains acetaminophen. Severe liver damage may occur if you take

- more than 4,000 mg of acetaminophen in 24 hours
- with other drugs containing acetaminophen
- 3 or more alcoholic drinks every day while using this product

Allergy alert: Acetaminophen may cause severe skin reactions. Symptoms may include:

- blisters
- rash
- skin reddening

If a skin reaction occurs, stop use and seek medical help right away.

Caffeine warning: The recommended dose of this product contains about as much caffeine as a cup of coffee. Limit the use of caffeine-containing medications, foods, or beverages while taking this product because too much caffeine may cause nervousness, irritability, sleeplessness, and, occasionally, rapid heartbeat.

Do not use

with any other drug containing acetaminophen (prescription or nonprescription). If you are not sure whether a drug contains acetaminophen, ask a doctor or pharmacist.

Ask a doctor before use if you have

liver disease.

Ask a doctor or pharmacist before use if you are

taking the blood thinning drug warfarin.

Stop use and ask a doctor if

- pain gets worse or lasts more than 10 days
- fever gets worse or lasts more than 3 days
- redness or swelling is present
- any new symptoms appear

If pregnant or breast-feeding,

ask a health professional before use.

Keep out of reach of children.

In case of overdose, get medical help or contact a Poison Control Center right away. Prompt medical attention is critical for adults as well as for children even if you do not notice any signs or symptoms.

Directions

- do not take more than directed
- adults and children 12 years and over: take 2 caplets every 6 hours. Do not take more than 6 caplets in 24 hours.
- children under 12 years: ask a doctor

Other information

- store at 25°C (77°F); excursions permitted between 15°-30°C (59°-86°F)
- use by expiration date on package

Inactive ingredients

corn starch, crospovidone, D&C red #27 aluminum lake, FD&C blue #2 aluminum lake, FD&C yellow #6 aluminum lake, magnesium stearate, microcrystalline cellulose, polyethylene glycol, polyvinyl alcohol, povidone, sodium starch glycolate, stearic acid, talc, titanium dioxide

Questions or comments?

1-800-426-9391

Principal Display Panel

♥︎CVS™

NDC 59779-824-21

actual size

Aspirin Free
TENSION HEADACHE
Acetaminophen, 500 mg
Caffeine, 65 mg
Pain Reliever, Pain Reliever Aid

Compare to Excedrin® Tension
Headache active ingredients*

100 CAPLETS

TAMPER EVIDENT: DO NOT USE IF IMPRINTED
SAFETY SEAL UNDER CAP IS BROKEN OR MISSING

*This product is not manufactured or distributed by Haleon
CH SARL, owner of the registered trademark Excedrin®
Tension Headache.

50844 ORG082442812

Distributed by:
CVS Pharmacy, Inc.
One CVS Drive
Woonsocket, RI 02895
© 2025 CVS/pharmacy
CVS.com®
1-800-SHOP CVS
V-11112

CVS 44-428